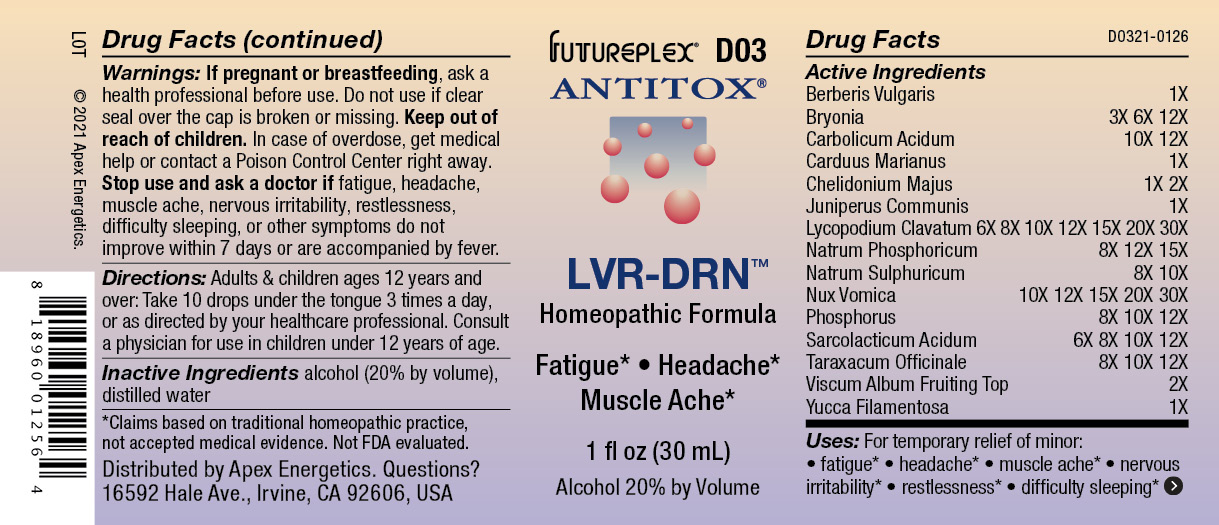 DRUG LABEL: D03
NDC: 63479-0403 | Form: SOLUTION
Manufacturer: Apex Energetics Inc.
Category: homeopathic | Type: HUMAN OTC DRUG LABEL
Date: 20240108

ACTIVE INGREDIENTS: BERBERIS VULGARIS ROOT BARK 1 [hp_X]/1 mL; BRYONIA ALBA ROOT 12 [hp_X]/1 mL; PHENOL 12 [hp_X]/1 mL; MILK THISTLE 1 [hp_X]/1 mL; CHELIDONIUM MAJUS 2 [hp_X]/1 mL; JUNIPER BERRY 1 [hp_X]/1 mL; LYCOPODIUM CLAVATUM SPORE 30 [hp_X]/1 mL; SODIUM PHOSPHATE, DIBASIC, HEPTAHYDRATE 15 [hp_X]/1 mL; SODIUM SULFATE 10 [hp_X]/1 mL; STRYCHNOS NUX-VOMICA SEED 30 [hp_X]/1 mL; PHOSPHORUS 12 [hp_X]/1 mL; LACTIC ACID, L- 12 [hp_X]/1 mL; TARAXACUM OFFICINALE 12 [hp_X]/1 mL; VISCUM ALBUM FRUITING TOP 2 [hp_X]/1 mL; YUCCA FILAMENTOSA 1 [hp_X]/1 mL
INACTIVE INGREDIENTS: ALCOHOL; WATER

D03

Active Ingredients
Berberis Vulgaris | 1X
Bryonia | 3X 6X 12X
Carbolicum Acidum | 10X 12X
Carduus Marianus | 1X
Chelidonium Majus | 1X 2X
Juniperus Communis | 1X
Lycopodium Clavatum | 6X 8X 10X 12X 15X 20X 30X
Natrum Phosphoricum | 8X 12X 15X
Natrum Sulphuricum | 8X 10X
Nux Vomica | 10X 12X 15X 20X 30X
Phosphorus | 8X 10X 12X
Sarcolacticum Acidum | 6X 8X 10X 12X
Taraxacum Officinale | 8X 10X 12X
Viscum Album Fruiting Top | 2X
Yucca Filamentosa | 1X

Uses:

PURPOSE

For temporary relief of minor:

fatigue*

headache*

muscle ache*

nervous irritability*

restlessness*

difficulty sleeping*

*Claims based on traditional homeopathic practice, not accepted medical evidence. Not FDA evaluated.

Warnings:

PREGNANCY OR BREAST FEEDING

If pregnant or breastfeeding, ask a health professional before use.

Do not use if clear seal over the cap is broken or missing.

Keep out of reach of children. In case of overdose, get medical help or contact a Poison Control Center right away.

Stop use and ask a doctor if fatigue, headache, muscle ache, nervous irritability, restlessness, difficulty sleeping, or other symptoms do not improve within 7 days or are accompanied by fever.

Directions:

Adults & children ages 12 years and over: Take 10 drops under the tongue 3 times a day, or as directed by your healthcare professional. Consult a physician for use in children under 12 years of age.

Inactive Ingredients

alcohol (20% by volume), distilled water

Distributed by Apex Energetics. Questions?
16592 Hale Ave., Irvine, CA 92606, USA

PACKAGE LABEL

FUTUREPLEX® D03

ANTITOX®

LVR-DRN™

Homeopathic Formula

Fatigue • Headache

Muscle Ache

1 fl oz (30 mL))

Alcohol 20% by Volume